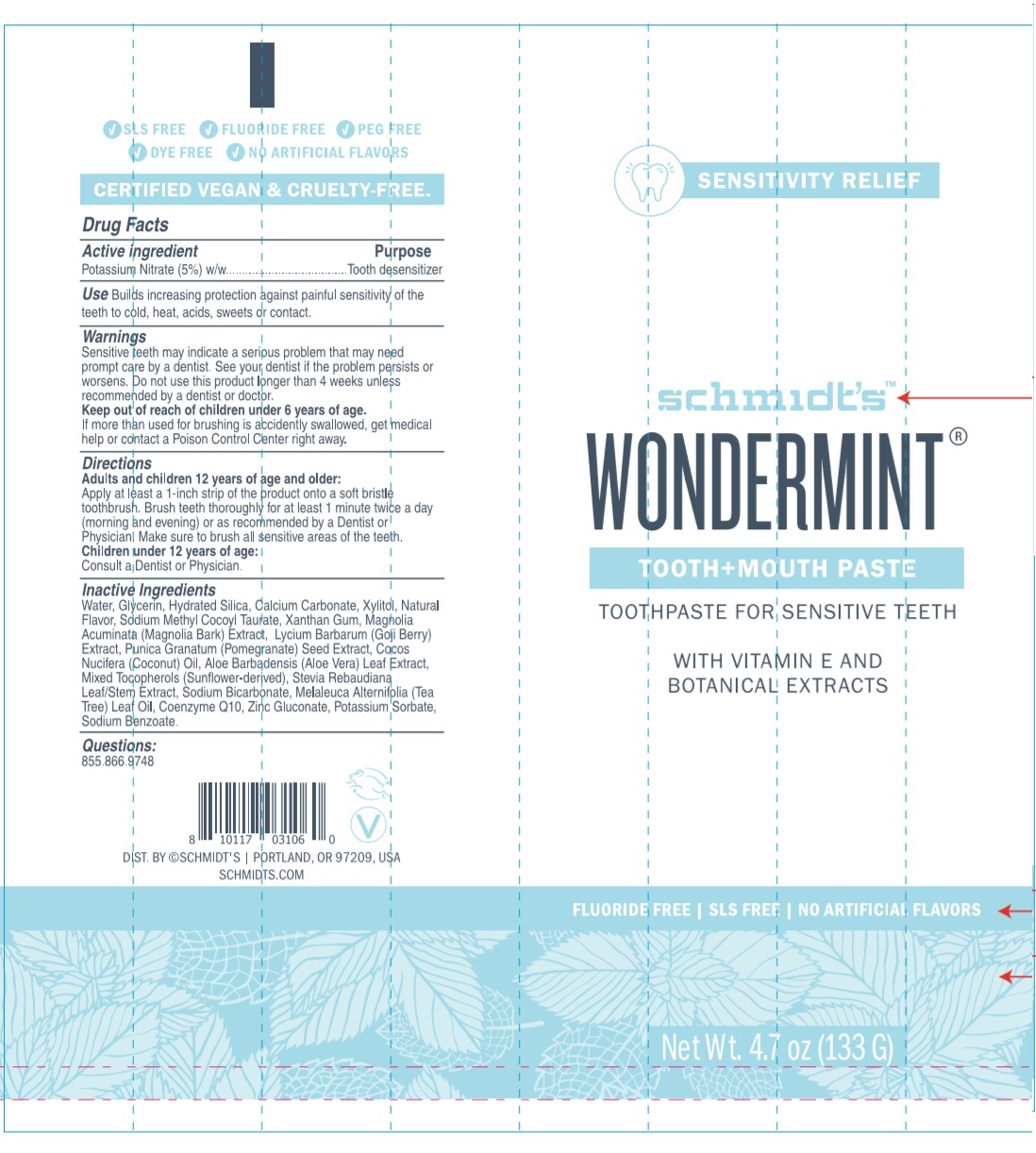 DRUG LABEL: Schmidts
NDC: 72916-210 | Form: PASTE, DENTIFRICE
Manufacturer: Schmidt's Naturals
Category: otc | Type: HUMAN OTC DRUG LABEL
Date: 20190613

ACTIVE INGREDIENTS: POTASSIUM NITRATE 6.662 g/133 g
INACTIVE INGREDIENTS: WATER; GLYCERIN; HYDRATED SILICA; CALCIUM CARBONATE; XYLITOL; SODIUM METHYL COCOYL TAURATE; XANTHAN GUM; MAGNOLIA ACUMINATA BARK; LYCIUM BARBARUM FRUIT; POMEGRANATE SEED; COCONUT OIL; ALOE VERA LEAF; TOCOPHEROL; STEVIA REBAUDIUNA LEAF; SODIUM BICARBONATE; TEA TREE OIL; UBIDECARENONE; ZINC GLUCONATE; POTASSIUM SORBATE; SODIUM BENZOATE

Schmidt's™-WONDERMINT® TOOTH+MOUTH PASTE

Active ingredient

Potassium Nitrate (5%) w/w

Purpose

Tooth desensitizer

Use

Builds increasing protection against painful sensitivity of the teeth to cold, heat, acids, sweets, or contact.

Warnings

Sensitive teeth may indicate a serious problem that may need prompt care by a dentist. See your dentist if the problem persists or worsens. Do not use this product longer than 4 weeks unless recommended by a dentist or doctor.

Keep out of reach of children under 6 years of age.
If more than used for brushing is accidentally swallowed, get medical help or contact a Poison Control Center right away.

Directions

Adults and children 12 years of age and older:
Apply at least a 1-inch strip of the product onto a soft bristle toothbrush. Brush teeth thoroughly for at least 1 minute twice a day (morning and evening) or as recommended by a Dentist or Physician. Make sure to brush all sensitive areas of the teeth.
Children under 12 years of age:
Consult a Dentist or Physician.

Inactive Ingredients

Water, Glycerin, Hydrated Silica, Calcium Carbonate, Xylitol, Natural Flavor, Sodium Methyl Cocoyl Taurate, Xanthan Gum, Magnolia Acuminata (Magnolia Bark) Extract, Lycium Barbarum (Goji Berry) Extract, Punica Granatum (Pomegranate) Seed Extract, Cocos Nucifera (Coconut) Oil, Aloe Barbadensis (Aloe Vera) Leaf Extract, Mixed Tocopherols (Sunflower-derived), Stevia Rebaudiana Leaf/Stem Extract, Sodium Bicarbonate, Melaleuca Alternifolia (Tea Tree) Leaf Oil, Coenzyme Q10, Zinc Gluconate, Potassium Sorbate, Sodium Benzoate.

Questions:

855.866.9748

SENSITIVITY RELIEF

TOOTHPASTE FOR SENSITIVE TEETH

WITH VITAMIN E AND BOTANICAL EXTRACTS

FLUORIDE FREE | SLS FREE | NO ARTIFICIAL FLAVORS

√ PEG FREE √ DYE FREE

CERTIFIED VEGAN & CRUELTY-FREE.

DIST. BY ©SCHMIDT'S | PORTLAND, OR 97209, USA
SCHMIDTS.COM